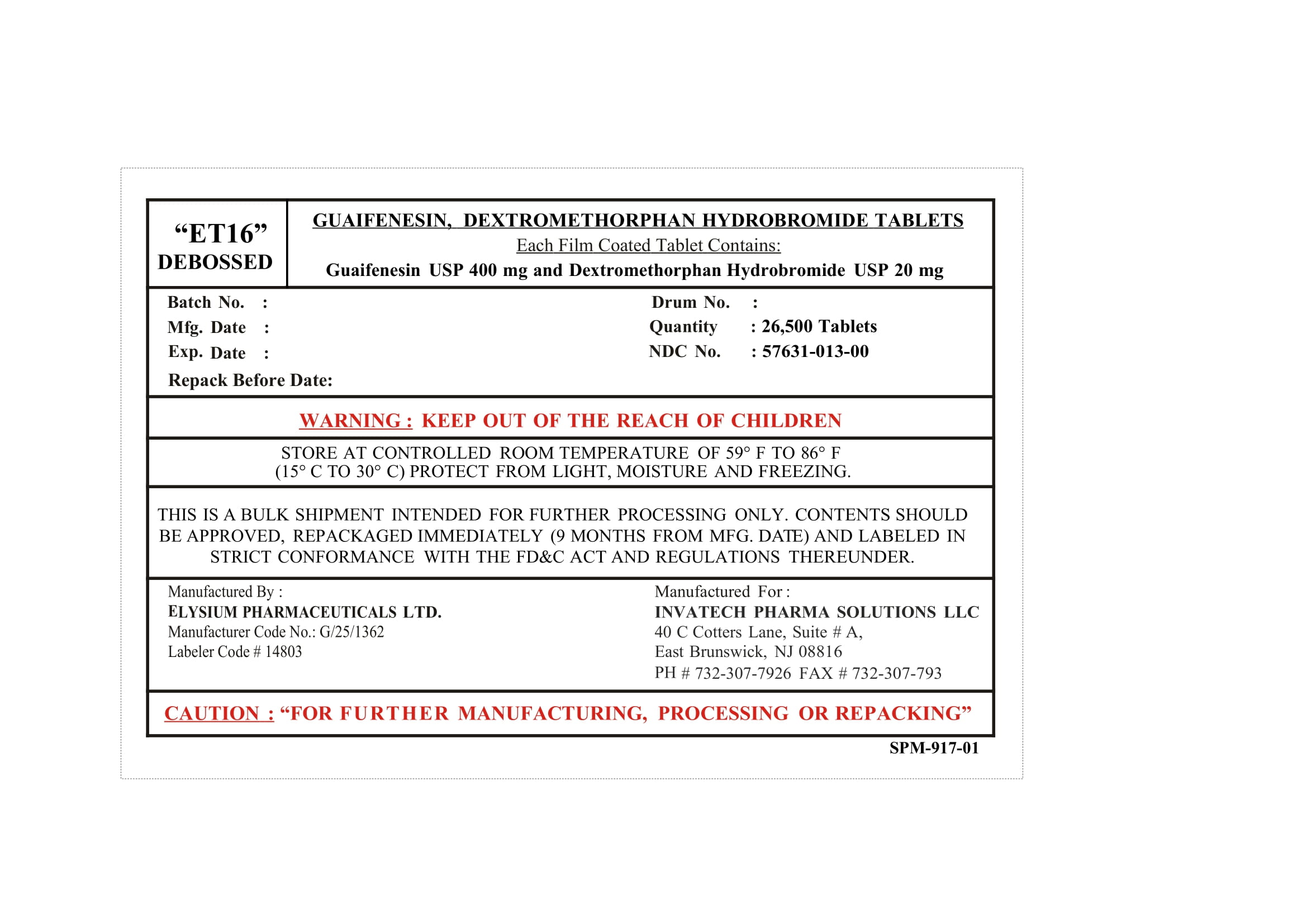 DRUG LABEL: Guaifenesin and Dextromethorphan Hydrobromide
NDC: 57631-013 | Form: TABLET
Manufacturer: InvaTech Pharma Solutions LLC
Category: otc | Type: HUMAN OTC DRUG LABEL
Date: 20251002

ACTIVE INGREDIENTS: GUAIFENESIN 400 mg/1 1; DEXTROMETHORPHAN HYDROBROMIDE 20 mg/1 1
INACTIVE INGREDIENTS: MAGNESIUM STEARATE; MALTODEXTRIN; POVIDONE K30; HYPROMELLOSES; SODIUM STARCH GLYCOLATE TYPE A; POLYETHYLENE GLYCOL 400; MICROCRYSTALLINE CELLULOSE; CROSCARMELLOSE SODIUM; SILICON DIOXIDE

Guaifenesin, Dextromethorphan Hydrobromide Tablets

PURPOSE

FOR FURTHER MANUFACTURING, PROCESSING OR REPACKING

KEEP OUT OF THE REACH OF CHILDREN

INDICATIONS AND USAGE

cough cold, allergic

WARNINGS

KEEP OUT OF THE REACH OF CHILDREN,FOR FURTHER MANUFACTURING, PROCESSING OR REPACKING

INACTIVE INGREDIENT

Colloidal Silicon Di oxide USP/NF, Hypromellose 5 [ Hydroxy propyl methyl cellulose - E5] USP, Hypromellose 15 Hydroxy propyl methylcellulose E-15 USP, Magnesium stearate. USP/NF, Maltodextrin USP/NF, Microcrystalline cellulose (PH-102) USP/NF, Polyethylene glycol 400 USP/NF, Polyvinyl pyrrolidone (PVPK 30) USP, Sodium starch glycolate Type-A USP/NF, Stearic acid powder